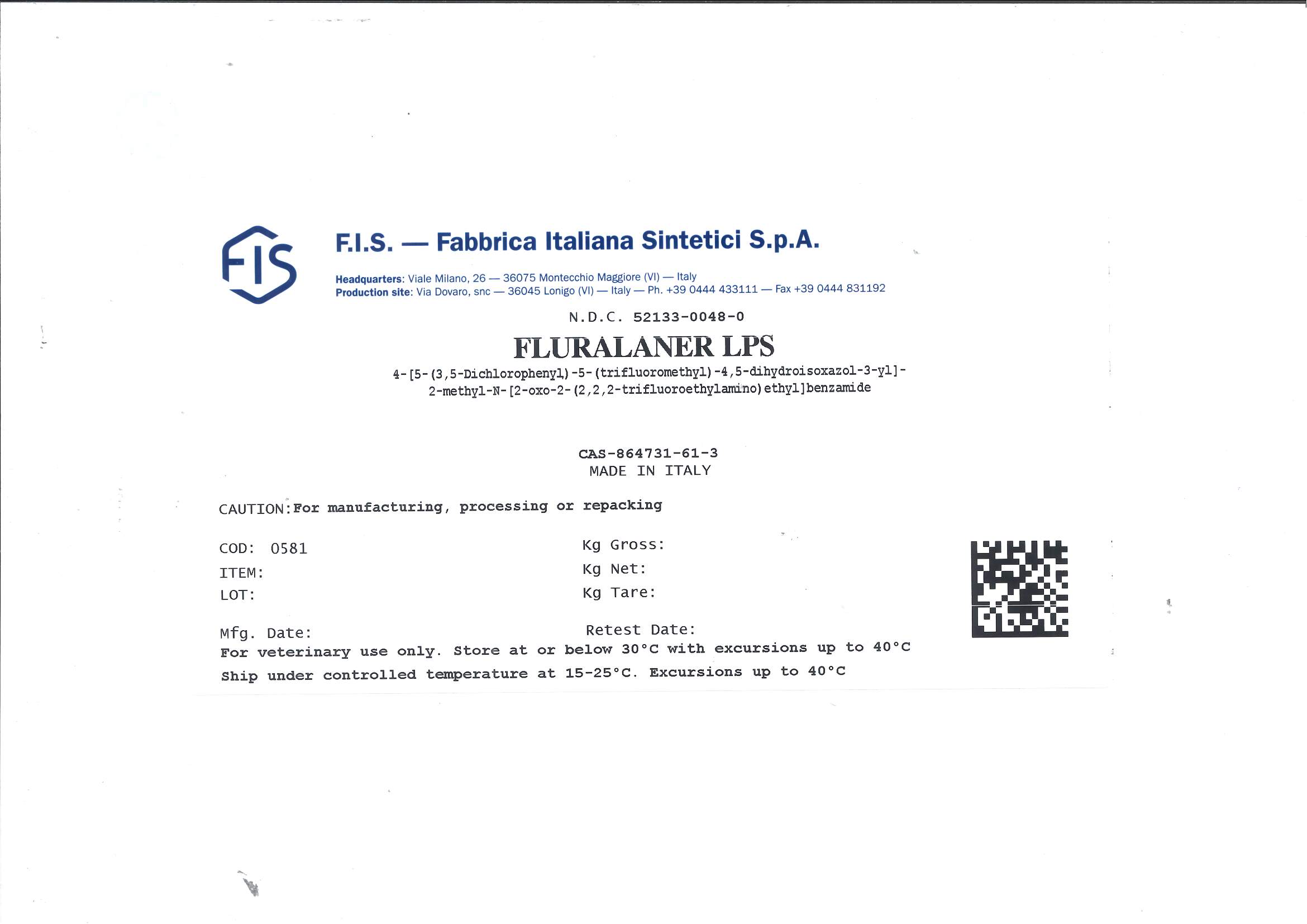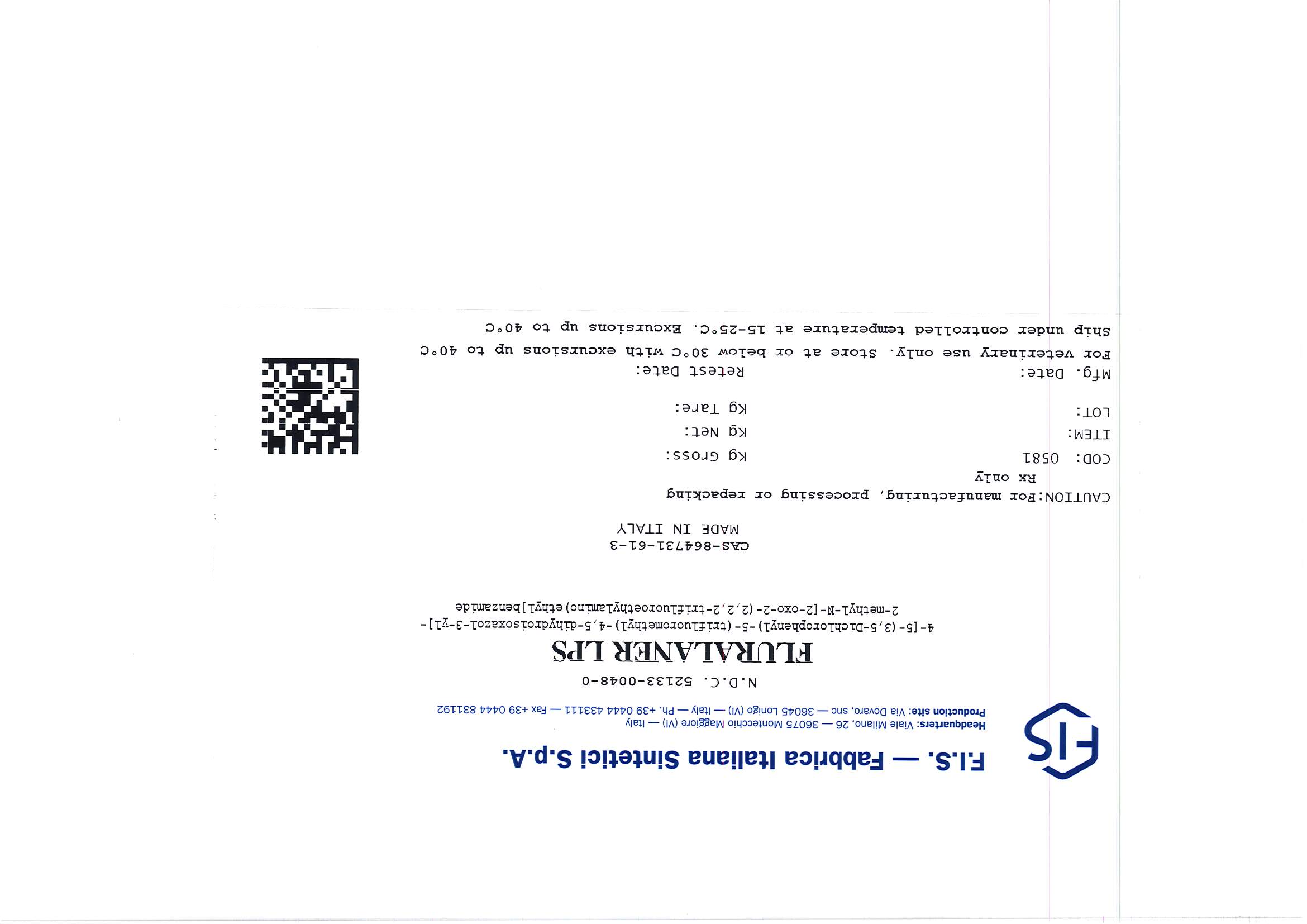 DRUG LABEL: Fluralaner LPS
NDC: 52133-0048 | Form: POWDER
Manufacturer: F.I.S. - Fabbrica Italiana Sintetici S.p.A.
Category: other | Type: BULK INGREDIENT - ANIMAL DRUG
Date: 20241028

ACTIVE INGREDIENTS: FLURALANER 1 kg/1 kg

Fluralaner LPS